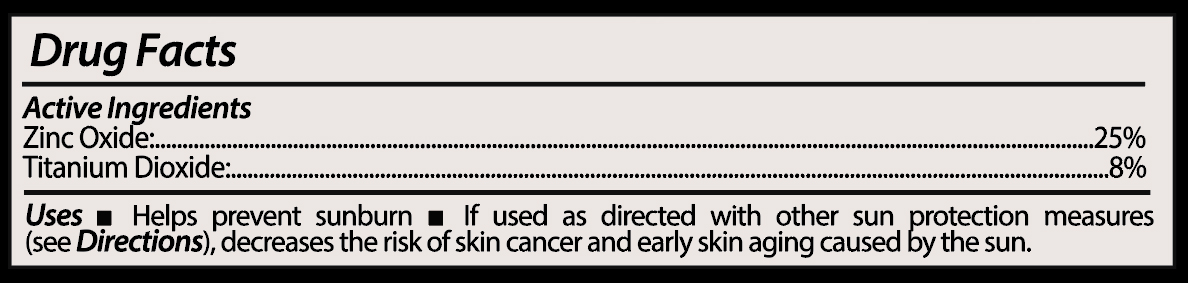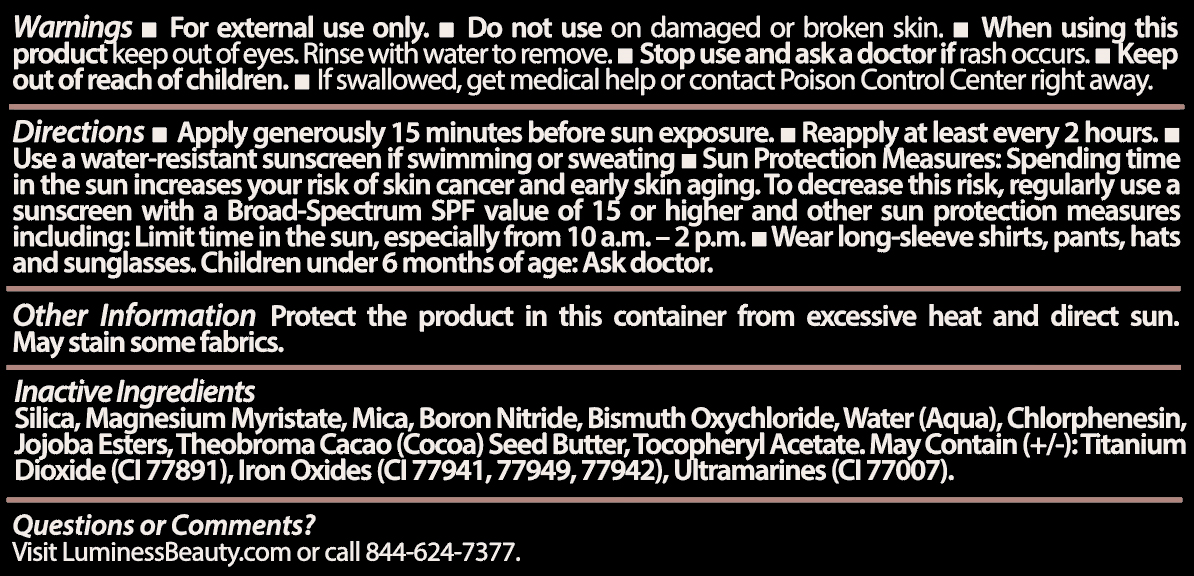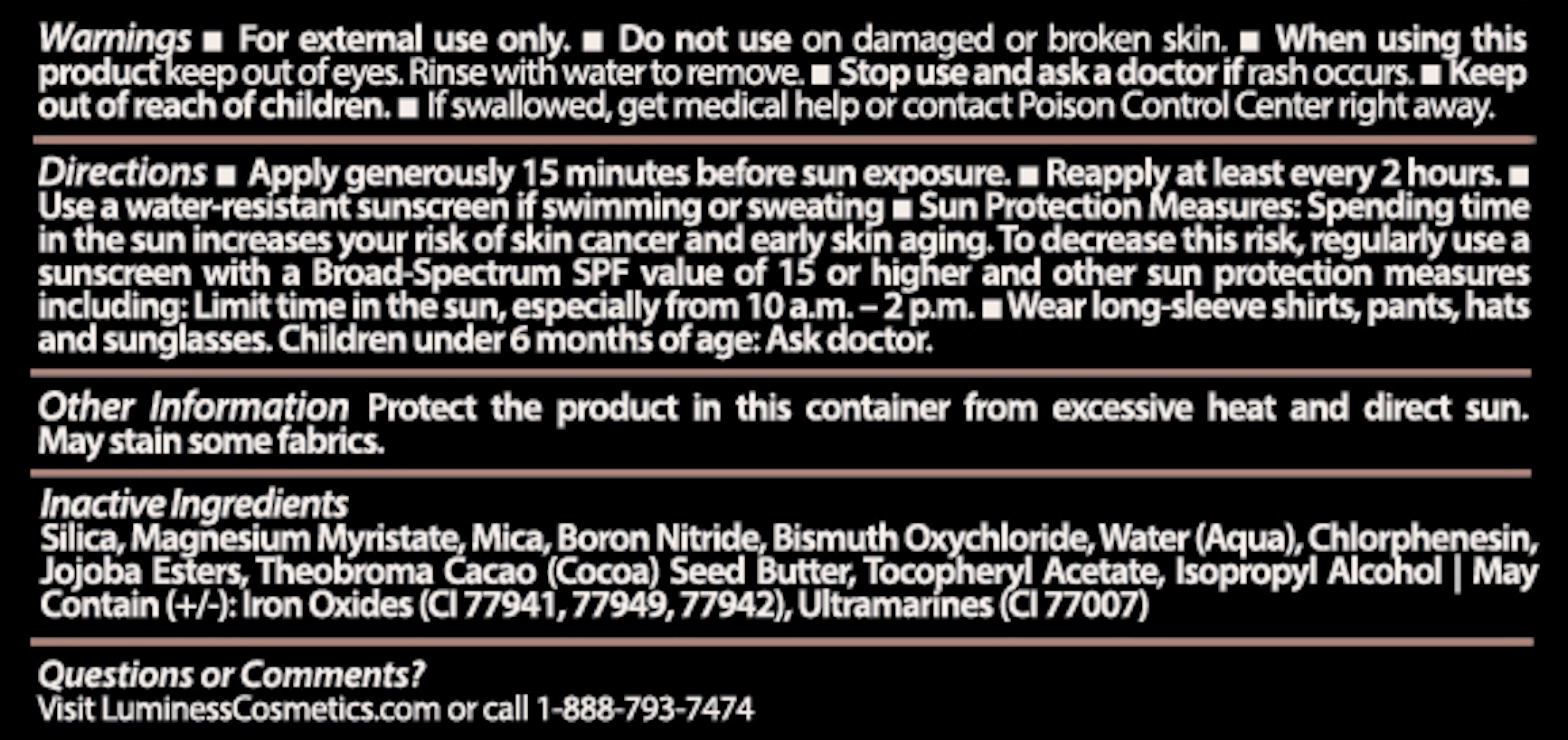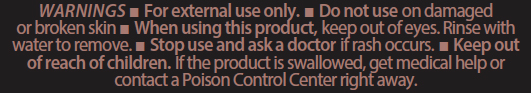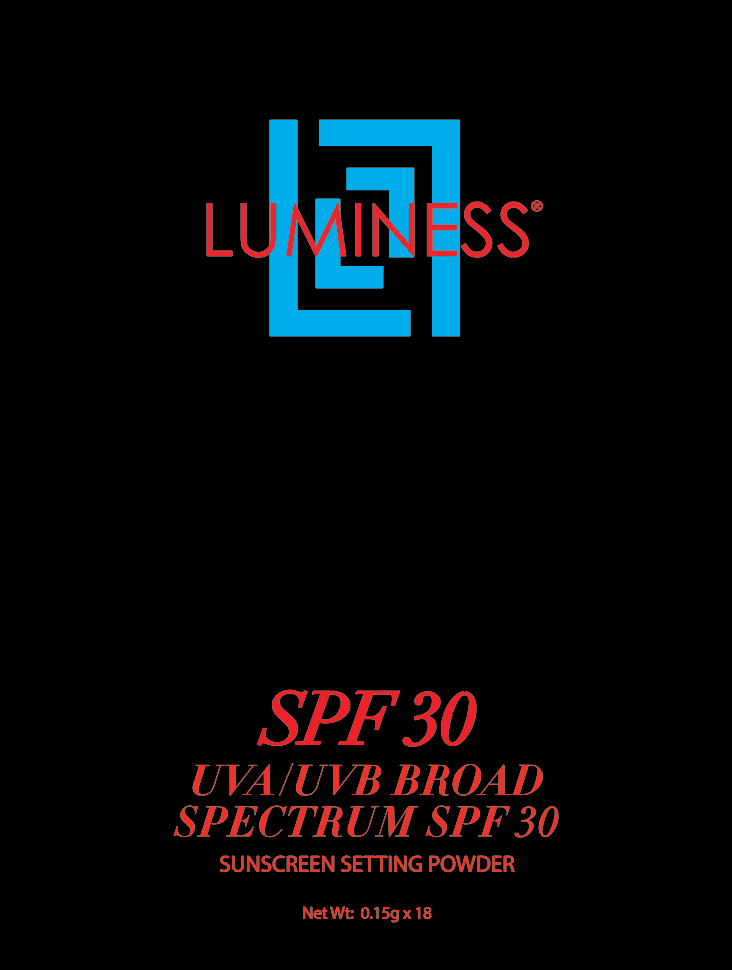 DRUG LABEL: Luminess SPF30 Suncreen Setting Powder
NDC: 73368-150 | Form: POWDER
Manufacturer: Kinetics Derma Beauty, L.L.C
Category: otc | Type: HUMAN OTC DRUG LABEL
Date: 20240612

ACTIVE INGREDIENTS: ZINC OXIDE 0.0375 g/0.15 g; TITANIUM DIOXIDE 0.012 g/0.15 g
INACTIVE INGREDIENTS: POTASSIUM HYDROLYZED JOJOBA ESTERS; BISMUTH OXYCHLORIDE; CHLORPHENESIN; .ALPHA.-TOCOPHEROL ACETATE, DL-; MAGNESIUM MYRISTATE; MICA; THEOBROMA GRANDIFLORUM SEED BUTTER; SILICON DIOXIDE; BORON NITRIDE; ISOPROPYL ALCOHOL

Luminess SPF 30 Suncreen Setting Powder